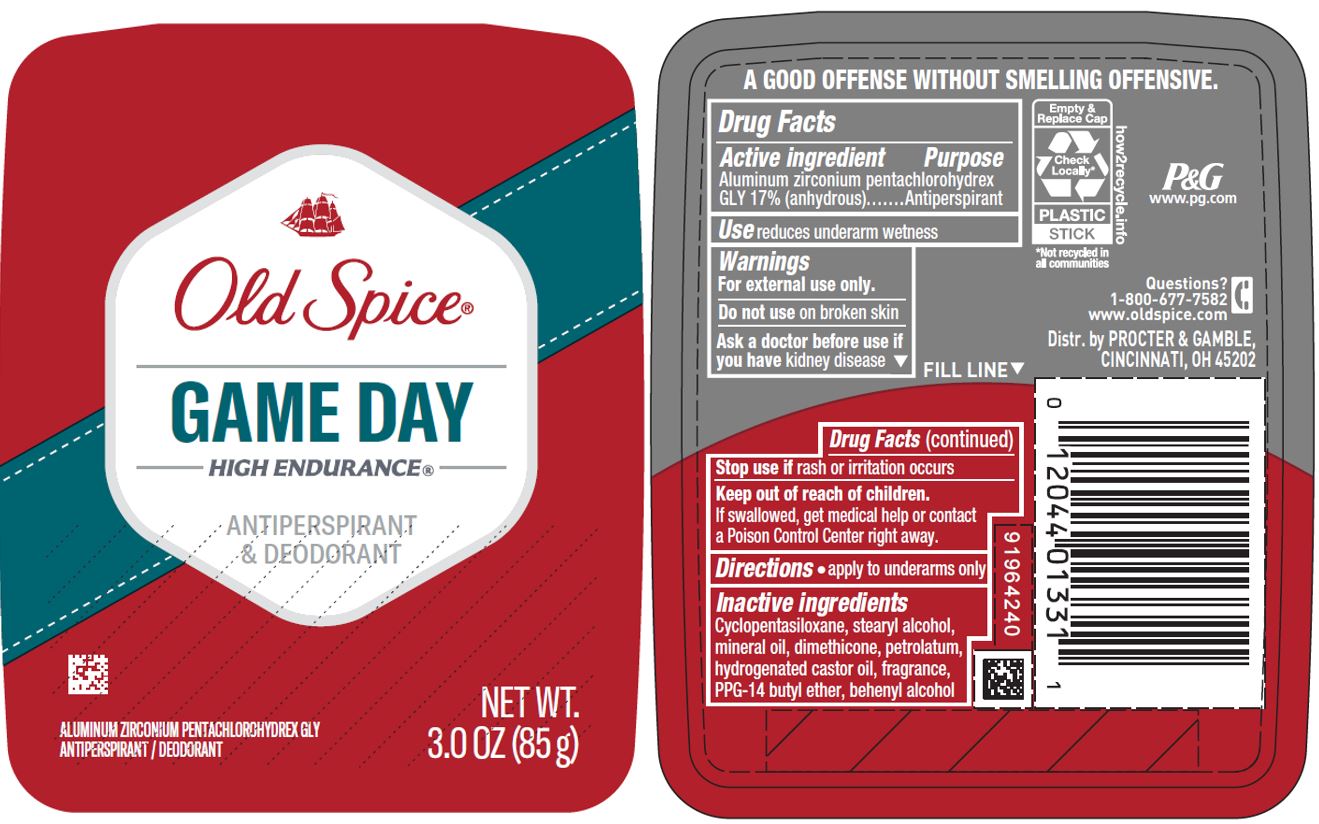 DRUG LABEL: Old Spice Game Day
NDC: 69423-596 | Form: STICK
Manufacturer: The Procter & Gamble Manufacturing Company
Category: otc | Type: HUMAN OTC DRUG LABEL
Date: 20251218

ACTIVE INGREDIENTS: ALUMINUM ZIRCONIUM PENTACHLOROHYDREX GLY 17 g/100 g
INACTIVE INGREDIENTS: .BETA.-CITRONELLOL, (R)-; CITRAL; 2-ETHYL-4-(2,2,3-TRIMETHYLCYCLOPENT-3-EN-1-YL)BUT-2-EN-1-OL; 2-ISOBUTYL-4-METHYLTETRAHYDROPYRAN-4-OL; COUMARIN; DIPROPYLENE GLYCOL; HEXAMETHYLINDANOPYRAN; ALLYL AMYL GLYCOLATE; LINALOOL, (+/-)-; LAVANDIN OIL; LINALYL ACETATE; METHYL IONONES; 3-(3,4-METHYLENEDIOXYPHENYL)-2-METHYLPROPANAL; TRIETHYL CITRATE; AMBROXIDE, (-)-; METHYL 3-METHYLORSELLINATE; ORANGE OIL; LEMON; LEMON OIL; CYCLAMEN ALDEHYDE; DIHYDRO PENTAMETHYLINDANONE; ETHYLENE BRASSYLATE; GERANYL ACETATE; .ALPHA.-HEXYLCINNAMALDEHYDE; ISOAMBRETTOLIDE; 4-ACETOXY-3-PENTYLTETRAHYDROPYRAN; PRECYCLEMONE B; TETRAMETHYL ACETYLOCTAHYDRONAPHTHALENES; STEARYL ALCOHOL; PPG-14 BUTYL ETHER; 3,5,5-TRIMETHYLHEXYL ACETATE; HYDROGENATED CASTOR OIL; PETROLATUM; MINERAL OIL; DOCOSANOL; DIMETHICONE; CYCLOMETHICONE 5; 8-(N-INDOLYL)-2,6-DIMETHYL-7-OCTEN-2-OL; ISOMETHYL-.ALPHA.-IONONE

Old Spice® Game Day
High Endurance® (new active)

Drug Facts

Active ingredient

Aluminum zirconium pentachlorohydrex Gly 17% (anhydrous)

Purpose

Antiperspirant

Use

reduces underarm wetness

Warnings

For external use only.

Do not use on broken skin

Ask a doctor before use if you have kidney disease

Stop use if rash or irritation occurs

Keep out of reach of children. If swallowed, get medical help or contact a Poison Control Center right away.

Directions

- apply to underarms only

Inactive ingredients

cyclopentasiloxane, stearyl alcohol, mineral oil, dimethicone, petrolatum, hydrogenated castor oil, fragrance, PPG-14 butyl ether, behenyl alcohol

Questions?

1-800-677-7582

Dist. by PROCTER & GAMBLE, CINCINNATI, OH 45202.

PRINCIPAL DISPLAY PANEL - 85 g Canister Label

Old Spice®

GAME DAY
HIGH ENDURANCE®

ANTIPERSPIRANT
& DEODORANT

Aluminum Zirconium Pentachlorohydrex Gly
ANTIPERSPIRANT/DEODORANT

NET WT. 3.0 OZ (85 g)